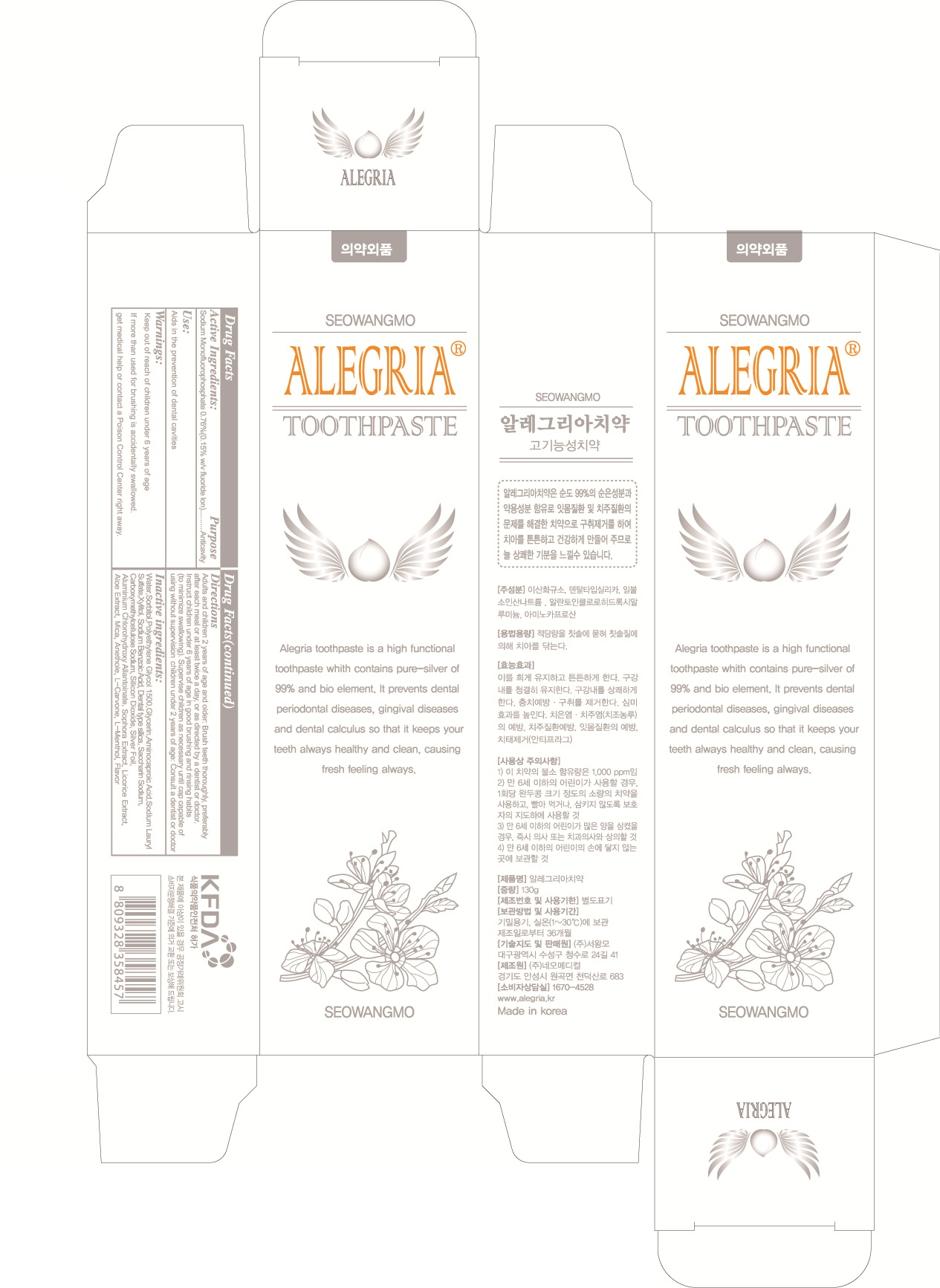 DRUG LABEL: ALEGRIA
NDC: 70406-010 | Form: PASTE, DENTIFRICE
Manufacturer: Seowangmo corporation
Category: otc | Type: HUMAN OTC DRUG LABEL
Date: 20160225

ACTIVE INGREDIENTS: Sodium Monofluorophosphate 0.98 g/130 g
INACTIVE INGREDIENTS: Silicon Dioxide; Glycerin

ACTIVE INGREDIENT

Active Ingredient: Sodium Monofluorophosphate 0.76%

INACTIVE INGREDIENT

Inactive Ingredients: D-Sorbitol Solution, Silicon Dioxide, Dentaltype silica, Polyethylene Glycol 1500, Glycerin, Sodium Lauryl Sulfate, Carboxymethylcellulose Sodium, Sodium Benzoate, Allantonie Chlorohydroxy Aluminum, Aminocaproic Acid, Xylitol, Saccharin Sodium Hydrate, Licorice Extract, Sophora Extract, Aloevera Gel, Peppermint Oil, L-Menthol, Anethole, Carvone, Mica, Silver foil, Purified Water

PURPOSE

Purpose: Anticavity

WARNINGS

Warnings: If more than used for brushing is accidentally swallowed, get medical help or contact a Poison Control Center right away.

Keep out of reach of children: Keep out of reach of children under 6 years of age.

Use

Use: Aids in the prevention of dental cavities

Directions

Directions: 1) Adults and children 2 years of age and older: Brush teeth throughly preferably after each meal or at least twice a day or as directed by a dentist or doctor. 2) Children under 6 years: To minimize swallowing, use a pea-sized amount and supervise brushing until good habits are established. 3) Children under 2 years: Consult a dentist or doctor.